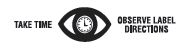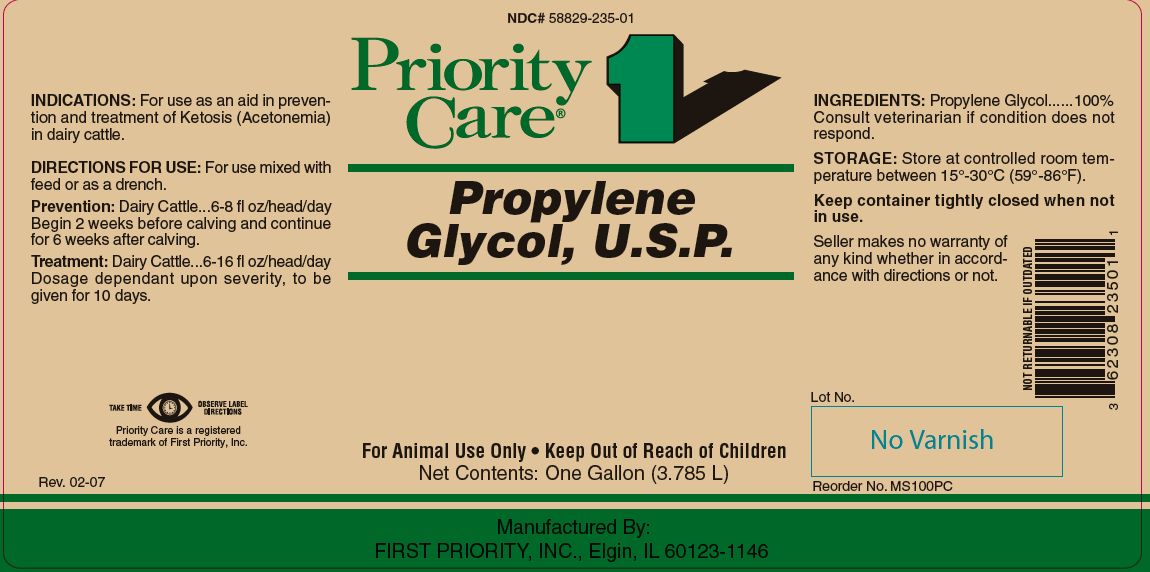 DRUG LABEL: PROPYLENE GLYCOL
NDC: 58829-235 | Form: LIQUID
Manufacturer: FIRST PRIORITY INCORPORATED
Category: animal | Type: OTC ANIMAL DRUG LABEL
Date: 20241028

ACTIVE INGREDIENTS: PROPYLENE GLYCOL 1034.2 g/1 L

PROPYLENE GLYCOL, U.S.P

KEEP OUT OF REACH OF CHILDREN

For Animal Use Only
Keep Out of Reach of Children

INDICATIONS:

For use as an aid in prevention and treatment of Ketosis (Acetonemia) in dairy cattle.

DIRECTIONS FOR USE:

For use mixed with feed or as a drench.

Prevention:

Dairy Cattle...6-8 fl oz/head/day
Begin 2 weeks before calving and continue for 6 weeks after calving.

Treatment:

Dairy Cattle...6-16 fl oz/head/day
Dosage dependant upon severity, to be given for 10 days.

INGREDIENTS:

Propylene Glycol .........................................100%

Consult veterinarian if condition does not respond.

STORAGE:

Store at controlled room temperature between 15º to 30ºC (59º-86ºF).

Keep container tightly closed when not in use.

INFORMATION FOR OWNERS/CAREGIVERS

Seller makes no warranty of any kind whether in accordance with directions or not.

Priority Care is a registered trademark of First Priority, Inc.

Manufactured By: FIRST PRIORITY, INC., Elgin, IL 60123-1146

NOT RETURNABLE IF OUTDATED